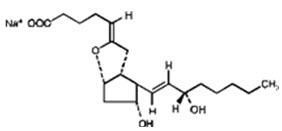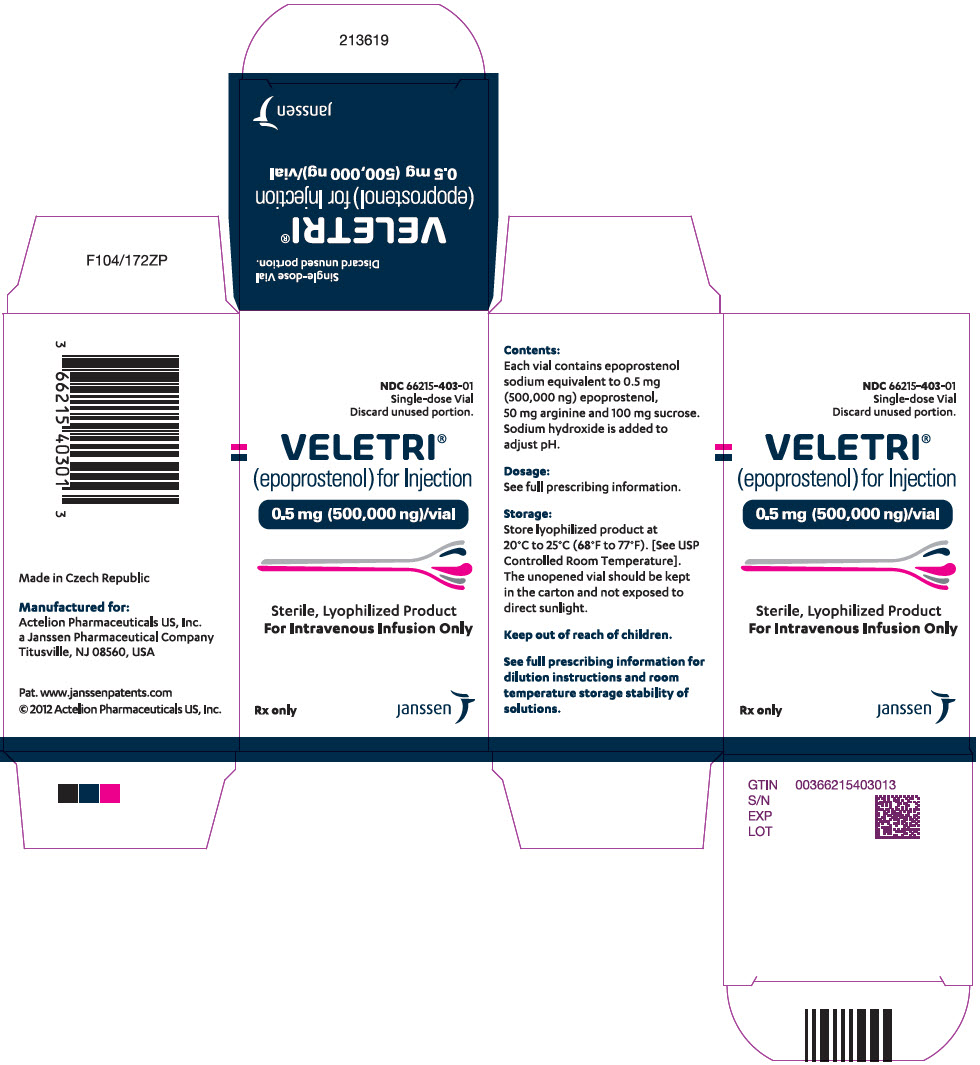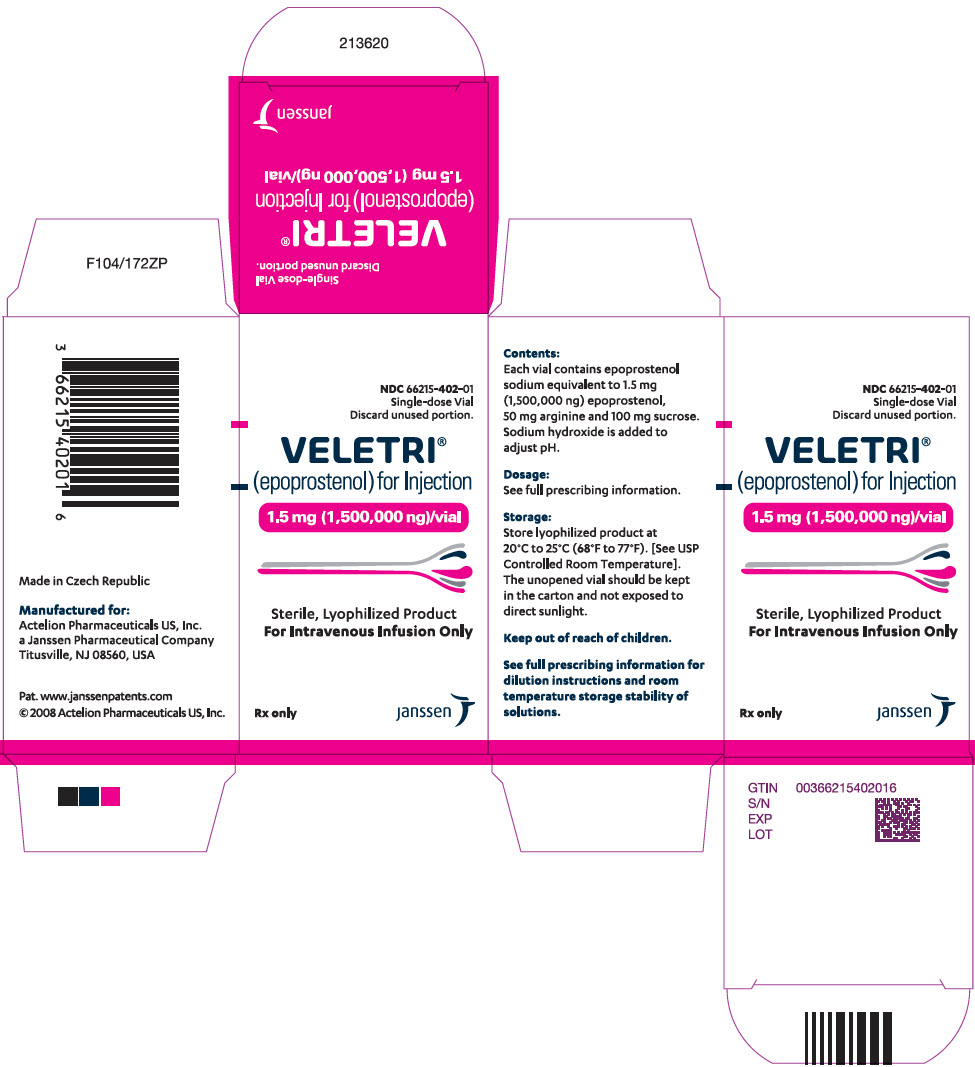 DRUG LABEL: Veletri
NDC: 66215-403 | Form: INJECTION, POWDER, LYOPHILIZED, FOR SOLUTION
Manufacturer: Actelion Pharmaceuticals US, Inc.
Category: prescription | Type: HUMAN PRESCRIPTION DRUG LABEL
Date: 20221128

ACTIVE INGREDIENTS: epoprostenol 0.5 mg/10 mL
INACTIVE INGREDIENTS: arginine; sucrose; sodium hydroxide

HIGHLIGHTS OF PRESCRIBING INFORMATION

These highlights do not include all the information needed to use VELETRI safely and effectively. See full prescribing information for VELETRI.
VELETRI® (epoprostenol) for injection, for intravenous use
Initial U.S. Approval: 1995

1 INDICATIONS AND USAGE

VELETRI is a prostacyclin vasodilator indicated for the treatment of pulmonary arterial hypertension (PAH) (WHO Group 1) to improve exercise capacity. Studies establishing effectiveness included predominantly patients with NYHA Functional Class III–IV symptoms and etiologies of idiopathic or heritable PAH or PAH associated with connective tissue diseases. (1)

2 DOSAGE AND ADMINISTRATION

- Dosage
  - Infusion of VELETRI should be initiated at 2 ng/kg/min and increased in increments of 2 ng/kg/min every 15 minutes or longer until dose-limiting pharmacologic effects are elicited or until a tolerance limit to the drug is established. (2.1)
  - If symptoms of pulmonary hypertension persist or recur after improving - the infusion should be increased by 1- to 2-ng/kg/min increments at intervals sufficient to allow assessment of clinical response; these intervals should be at least 15 minutes. (2.2)
- Administration
  - VELETRI is administered by continuous intravenous infusion via a central venous catheter using an ambulatory infusion pump. (2.3)
  - Do not mix with any other parenteral medications or solutions prior to or during administration. (2.4)
- Reconstitution
  - Reconstituted in vial with only 5 mL of either Sterile Water for Injection or Sodium Chloride 0.9% Injection.
  - VELETRI solution reconstituted and immediately diluted to the final concentration in the drug delivery reservoir can be administered per the conditions of use as outlined in Table 1. (2.4)
  - Solution for chronic delivery should be prepared in a drug delivery reservoir appropriate for the infusion pump. (2.4)

3 DOSAGE FORMS AND STRENGTHS

Injection: 10 mL single-dose vial with 0.5 mg (500,000 ng) or 1.5 mg (1,500,000 ng) VELETRI. (3)

4 CONTRAINDICATIONS

- Congestive heart failure due to severe left ventricular systolic dysfunction (4)
- Pulmonary edema (4)
- Hypersensitivity to the drug or to structurally related compounds (4)

5 WARNINGS AND PRECAUTIONS

- Do not abruptly lower the dose or withdraw dosing. All dosing initiation and changes should be closely monitored. (5.2, 5.3)

6 ADVERSE REACTIONS

- Most common adverse reactions during:
  - Dose Initiation and Escalation: Nausea, vomiting, headache, hypotension, flushing, chest pain, anxiety, dizziness, bradycardia, dyspnea, abdominal pain, musculoskeletal pain, and tachycardia (6.1)
  - Chronic Dosing: Headache, jaw pain, flushing, diarrhea, nausea and vomiting, flu-like symptoms, and anxiety/nervousness (6.1)

To report SUSPECTED ADVERSE REACTIONS, please contact: JANSSEN at 1-800-526-7736 (1-800 JANSSEN) or FDA at 1-800-FDA-1088, or www.fda.gov/medwatch.

7 DRUG INTERACTIONS

- Diuretics, antihypertensive agents, or other vasodilators: reduction in blood pressure (7)
- Antiplatelet agents or anticoagulants: increase the risk of bleeding (7)
- Patients on digoxin: elevations of digoxin concentrations clinically significant in patients prone to digoxin toxicity (7)

FULL PRESCRIBING INFORMATION

1 INDICATIONS AND USAGE

VELETRI is indicated for the treatment of pulmonary arterial hypertension (PAH) (WHO Group 1) to improve exercise capacity. Studies establishing effectiveness included predominantly patients with NYHA Functional Class III–IV symptoms and etiologies of idiopathic or heritable PAH or PAH associated with connective tissue diseases.

2 DOSAGE AND ADMINISTRATION

Important Note: Reconstitute VELETRI only as directed with Sterile Water for Injection, USP, or Sodium Chloride 0.9% Injection, USP. Do not dilute reconstituted solutions of VELETRI or administer it with other parenteral solutions or medications [see Dosage and Administration (2.4)].

2.1 Dosage

Prepare continuous chronic infusion of VELETRI as directed, and administer through a central venous catheter. Temporary peripheral intravenous infusion may be used until central access is established. Initiate chronic infusion of VELETRI at 2 ng/kg/min and increase in increments of 2 ng/kg/min every 15 minutes or longer until a tolerance limit to the drug is established or further increases in the infusion rate are not clinically warranted. If dose-limiting pharmacologic effects occur, then decrease the infusion rate until VELETRI is tolerated. In clinical trials, the most common dose-limiting adverse events were nausea, vomiting, hypotension, sepsis, headache, abdominal pain, or respiratory disorder (most treatment-limiting adverse events were not serious). If the initial infusion rate of 2 ng/kg/min is not tolerated, use a lower dose.

In the controlled 12-week trial in PAH/SSD, for example, the dose increased from a mean starting dose of 2.2 ng/kg/min. During the first 7 days of treatment, the dose was increased daily to a mean dose of 4.1 ng/kg/min on day 7 of treatment. At the end of week 12, the mean dose was 11.2 ng/kg/min. The mean incremental increase was 2 to 3 ng/kg/min every 3 weeks.

2.2 Dosage Adjustments

Base changes in the chronic infusion rate on persistence, recurrence, or worsening of the patient's symptoms of pulmonary hypertension and the occurrence of adverse events due to excessive doses of VELETRI. In general, expect increases in dose from the initial chronic dose.

Consider increments in dose if symptoms of pulmonary hypertension persist or recur. Adjust the infusion by 1- to 2-ng/kg/min increments at intervals sufficient to allow assessment of clinical response; these intervals should be at least 15 minutes. In clinical trials, incremental increases in dose occurred at intervals of 24 to 48 hours or longer. Following establishment of new chronic infusion rate, observe the patient, and monitor standing and supine blood pressure and heart rate for several hours to ensure that the new dose is tolerated.

During chronic infusion, the occurrence of dose-limiting pharmacological events may necessitate a decrease in infusion rate, but the adverse event may occasionally resolve without dosage adjustment. Make dosage decreases gradually in 2-ng/kg/min decrements every 15 minutes or longer until the dose-limiting effects resolve [see Adverse Reactions (6.1 and 6.2)]. Avoid abrupt withdrawal of VELETRI or sudden large reductions in infusion rates. Except in life-threatening situations (e.g., unconsciousness, collapse, etc.), infusion rates of VELETRI should be adjusted only under the direction of a physician.

In patients receiving lung transplants, doses of epoprostenol were tapered after the initiation of cardiopulmonary bypass.

2.3 Administration

VELETRI, once prepared as directed [see Dosage and Administration (2.4)], is administered by continuous intravenous infusion via a central venous catheter using an ambulatory infusion pump. During initiation of treatment, VELETRI may be administered peripherally.

Infusion sets with an in-line 0.22 micron filter should be used.

The ambulatory infusion pump used to administer VELETRI should: (1) be small and lightweight, (2) be able to adjust infusion rates in 2-ng/kg/min increments, (3) have occlusion, end-of-infusion, and low-battery alarms, (4) be accurate to ±6% of the programmed rate, and (5) be positive pressure-driven (continuous or pulsatile) with intervals between pulses not exceeding 3 minutes at infusion rates used to deliver VELETRI. The reservoir should be made of polyvinyl chloride, polypropylene, or glass. The infusion pump used in the most recent clinical trials was the CADD-1 HFX 5100 (SIMS Deltec). A 60-inch microbore non-DEHP extension set with proximal antisyphon valve, low priming volume (0.9 mL), and in-line 0.22 micron filter was used during clinical trials.

To avoid potential interruptions in drug delivery, the patient should have access to a backup infusion pump and intravenous infusion sets. Consider a multi-lumen catheter if other intravenous therapies are routinely administered.

2.4 Reconstitution

VELETRI is stable only when reconstituted as directed using Sterile Water for Injection, USP, or Sodium Chloride 0.9% Injection, USP. Do not reconstitute or mix VELETRI with any other parenteral medications or solutions prior to or during administration. Each vial is for single-dose; discard any unused solution.

Use after reconstitution and immediate dilution to final concentration.

Use at room temperature (77°F/25°C)

VELETRI solution reconstituted with 5 mL of Sterile Water for Injection, USP or Sodium Chloride 0.9% Injection, and immediately diluted to the final concentration in the drug delivery reservoir can be administered at room temperature per the conditions of use as outlined in Table 1.

Table 1: Maximum Duration of Administration (hours) at Room Temperature (77°F/ 25°C) of Fully Diluted Solutions in the Drug Delivery Reservoir [Short excursions at 104°F (40°C) are permitted for up to: 2 hours for concentrations below 15,000 ng/mL 4 hours for concentrations between 15,000 ng/mL and 60,000 ng/mL 8 hours for concentrations above 60,000 ng/mL]
Final concentration range | Immediate administration | If stored for up to 8 days at 36° to 46°F (2° to 8°C)
0.5 mg vial
≥3,000 ng/mL and <15,000 ng/mL | 48 hours | 24 hours
1.5 mg vial
≥15,000 ng/mL and <60,000 ng/mL | 48 hours | 48 hours
≥60,000 ng/mL | 72 hours | 48 hours

Use at higher temperatures >77°F up to 104°F (>25° to 40°C)

Temperatures greater than 77°F and up to 86°F (>25°C to 30°C): A single reservoir of fully diluted solution of 60,000 ng/mL or above of VELETRI prepared as directed can be administered (either immediately or after up to 8 days storage at 36° to 46°F (2° to 8°C)) for up to 48 hours. For diluted solutions of less than 60,000 ng/mL, pump reservoirs should be changed every 24 hours.

Temperatures up to 104°F (40°C): Fully diluted solutions of 60,000 ng/mL or above of VELETRI, prepared as directed, can be immediately administered for periods up to 24 hours.

Do not expose this solution to direct sunlight.

A concentration for the solution of VELETRI should be selected that is compatible with the infusion pump being used with respect to minimum and maximum flow rates, reservoir capacity, and the infusion pump criteria listed above. VELETRI, when administered chronically, should be prepared in a drug delivery reservoir appropriate for the infusion pump. Outlined in Table 2 are directions for preparing different concentrations of VELETRI.

Each vial is for single-dose; discard any unused solution.

Table 2: Reconstitution and Dilution Instructions
To make 100 mL of solution with Final Concentration (ng/mL) of: | Directions
Using the 0.5 mg vial
3,000 ng/ml | Dissolve contents of one 0.5 mg vial with 5 mL of Sterile Water for Injection, USP or Sodium Chloride 0.9% Injection, USP. Withdraw 3 mL of the vial contents and add to a sufficient volume of the identical diluent to make a total of 100 mL.
5,000 ng/mL | Dissolve contents of one 0.5 mg vial with 5 mL of Sterile Water for Injection, USP, or Sodium Chloride 0.9% Injection, USP. Withdraw entire vial contents and add to a sufficient volume of the identical diluent to make a total of 100 mL.
10,000 ng/mL | Dissolve contents of two 0.5 mg vials each with 5 mL of Sterile Water for Injection, USP, or Sodium Chloride 0.9% Injection, USP. Withdraw entire vial contents and add to a sufficient volume of the identical diluent to make a total of 100 mL.
Using the 1.5 mg vial
15,000 ng/mL [Higher concentrations may be prepared for patients who receive VELETRI long-term.] | Dissolve contents of one 1.5 mg vial with 5 mL of Sterile Water for Injection, USP, or Sodium Chloride 0.9% Injection, USP. Withdraw entire vial contents and add to a sufficient volume of the identical diluent to make a total of 100 mL.
30,000 ng/mL | Dissolve contents of two 1.5 mg vials each with 5 mL of Sterile Water for Injection, USP, or Sodium Chloride 0.9% Injection, USP. Withdraw entire vial contents and add to a sufficient volume of the identical diluent to make a total of 100 mL.

Infusion rates may be calculated using the following formula:

Infusion Rate (mL/hr)= | [Dose (ng/kg/min)×Weight (kg)×60 min/hr]
Infusion Rate (mL/hr)= | Final Concentration (ng/mL)

Tables 3 to 7 provide infusion delivery rates for doses up to 16 ng/kg/min based upon patient weight, drug delivery rate, and concentration of the solution of VELETRI to be used. These tables may be used to select the most appropriate concentration of VELETRI that will result in an infusion rate between the minimum and maximum flow rates of the infusion pump and that will allow the desired duration of infusion from a given reservoir volume. For infusion/dose rates lower than those listed in Tables 3 to 7, it is recommended that the pump rate be set by a healthcare professional such that steady state is achieved in the patient, keeping in mind the half-life of epoprostenol is no more than six minutes. Higher infusion rates, and therefore, more concentrated solutions may be necessary with long-term administration of VELETRI.

Table 3: Infusion Rates for VELETRI at a Concentration of 3,000 ng/mL
Patient weight (kg) | Dose or Drug Delivery Rate (ng/kg/min)
 | 2 | 3 | 4 | 5
 | Infusion Delivery Rate (mL/hr)
20 | – | 1.2 | 1.6 | 2.0
30 | 1.2 | 1.8 | 2.4 | 3.0
40 | 1.6 | 2.4 | 3.2 | 4.0
50 | 2.0 | 3.0 | 4.0 | –
60 | 2.4 | 3.6 | – | –
70 | 2.8 | – | – | –
80 | 3.2 | – | – | –
90 | 3.6 | – | – | –
100 | 4.0 | – | – | –

Table 4: Infusion Rates for VELETRI at a Concentration of 5,000 ng/mL
Patient weight (kg) | Dose or Drug Delivery Rate (ng/kg/min)
Patient weight (kg) | 2 | 4 | 6 | 8 | 10 | 12 | 14
 | Infusion Delivery Rate (mL/hr)
20 | – | 1.0 | 1.4 | 1.9 | 2.4 | 2.9 | 3.4
30 | – | 1.4 | 2.2 | 2.9 | 3.6 | – | –
40 | 1.0 | 1.9 | 2.9 | 3.8 | – | – | –
50 | 1.2 | 2.4 | 3.6 | – | – | – | –
60 | 1.4 | 2.9 | – | – | – | – | –
70 | 1.7 | 3.4 | – | – | – | – | –
80 | 1.9 | 3.8 | – | – | – | – | –
90 | 2.2 | – | – | – | – | – | –
100 | 2.4 | – | – | – | – | – | –

Table 5: Infusion Rates for VELETRI at a Concentration of 10,000 ng/mL
Patient weight (kg) | Dose or Drug Delivery Rate (ng/kg/min)
Patient weight (kg) | 4 | 6 | 8 | 10 | 12 | 14 | 16
 | Infusion Delivery Rate (mL/hr)
20 | – | – | 1.0 | 1.2 | 1.4 | 1.7 | 1.9
30 | – | 1.1 | 1.4 | 1.8 | 2.2 | 2.5 | 2.9
40 | 1.0 | 1.4 | 1.9 | 2.4 | 2.9 | 3.4 | 3.8
50 | 1.2 | 1.8 | 2.4 | 3.0 | 3.6 | – | –
60 | 1.4 | 2.2 | 2.9 | 3.6 | – | – | –
70 | 1.7 | 2.5 | 3.4 | – | – | – | –
80 | 1.9 | 2.9 | 3.8 | – | – | – | –
90 | 2.2 | 3.2 | – | – | – | – | –
100 | 2.4 | 3.6 | – | – | – | – | –

Table 6: Infusion Rates for VELETRI at a Concentration of 15,000 ng/mL
Patient weight (kg) | Dose or Drug Delivery Rate (ng/kg/min)
Patient weight (kg) | 4 | 6 | 8 | 10 | 12 | 14 | 16
 | Infusion Delivery Rate (mL/hr)
20 | – | – | – | – | 1.0 | 1.1 | 1.3
30 | – | – | 1.0 | 1.2 | 1.4 | 1.7 | 1.9
40 | – | 1.0 | 1.3 | 1.6 | 1.9 | 2.2 | 2.6
50 | – | 1.2 | 1.6 | 2.0 | 2.4 | 2.8 | 3.2
60 | 1.0 | 1.4 | 1.9 | 2.4 | 2.9 | 3.4 | 3.8
70 | 1.1 | 1.7 | 2.2 | 2.8 | 3.4 | 3.9 | –
80 | 1.3 | 1.9 | 2.6 | 3.2 | 3.8 | – | –
90 | 1.4 | 2.2 | 2.9 | 3.6 | – | – | –
100 | 1.6 | 2.4 | 3.2 | 4.0 | – | – | –

Table 7: Infusion Rates for VELETRI at a Concentration of 30,000 ng/mL
Patient weight (kg) | Dose or Drug Delivery Rate (ng/kg/min)
 | 6 | 8 | 10 | 12 | 14 | 16
30 | – | – | – | – | – | 1.0
40 | – | – | – | 1.0 | 1.1 | 1.3
50 | – | – | 1.0 | 1.2 | 1.4 | 1.6
60 | – | 1.0 | 1.2 | 1.4 | 1.7 | 1.9
70 | – | 1.1 | 1.4 | 1.7 | 2.0 | 2.2
80 | 1.0 | 1.3 | 1.6 | 1.9 | 2.2 | 2.6
90 | 1.1 | 1.4 | 1.8 | 2.2 | 2.5 | 2.9
100 | 1.2 | 1.6 | 2.0 | 2.4 | 2.8 | 3.2

3 DOSAGE FORMS AND STRENGTHS

VELETRI contains epoprostenol sodium equivalent to 0.5 mg (500,000 ng) or 1.5 mg (1,500,000 ng) epoprostenol and is supplied as a sterile lyophilized material in a 10 mL vial.

4 CONTRAINDICATIONS

A large study evaluating the effect of epoprostenol on survival in NYHA Class III and IV patients with congestive heart failure due to severe left ventricular systolic dysfunction was terminated after an interim analysis of 471 patients revealed a higher mortality in patients receiving epoprostenol plus conventional therapy than in those receiving conventional therapy alone. The chronic use of VELETRI in patients with congestive heart failure due to severe left ventricular systolic dysfunction is therefore contraindicated.

Some patients with pulmonary hypertension have developed pulmonary edema during dose initiation, which may be associated with pulmonary veno-occlusive disease. VELETRI should not be used chronically in patients who develop pulmonary edema during dose initiation.

VELETRI is also contraindicated in patients with known hypersensitivity to the drug or to structurally related compounds.

5 WARNINGS AND PRECAUTIONS

5.1 Dose Initiation

VELETRI is a potent pulmonary and systemic vasodilator. Initiate VELETRI in a setting with adequate personnel and equipment for physiologic monitoring and emergency care. Dose initiation has been performed during right heart catheterization and without cardiac catheterization. During dose initiation, asymptomatic increases in pulmonary artery pressure coincident with increases in cardiac output occurred rarely. In such cases, consider dose reduction, but such an increase does not imply that chronic treatment is contraindicated.

5.2 Chronic Use and Dose Adjustment

During chronic use, deliver VELETRI continuously on an ambulatory basis through a permanent indwelling central venous catheter. Unless contraindicated, administer anticoagulant therapy to patients receiving VELETRI to reduce the risk of pulmonary thromboembolism or systemic embolism through a patent foramen ovale. To reduce the risk of infection, use aseptic technique in the reconstitution and administration of VELETRI and in routine catheter care. Because epoprostenol is metabolized rapidly, even brief interruptions in the delivery of VELETRI may result in symptoms associated with rebound pulmonary hypertension including dyspnea, dizziness, and asthenia. Intravenous therapy with VELETRI will likely be needed for prolonged periods, possibly years, so consider the patient's capacity to accept and care for a permanent intravenous catheter and infusion pump.

Based on clinical trials, the acute hemodynamic response (reduction in pulmonary artery resistance) to epoprostenol did not correlate well with improvement in exercise tolerance or survival during chronic use of epoprostenol. Adjust dosage of VELETRI during chronic use at the first sign of recurrence or worsening of symptoms attributable to pulmonary hypertension or the occurrence of adverse events associated with epoprostenol [see Dosage and Administration (2.2)]. Following dosage adjustments, monitor standing and supine blood pressure and heart rate closely for several hours.

5.3 Withdrawal Effects

Abrupt withdrawal (including interruptions in drug delivery) or sudden large reductions in dosage of VELETRI may result in symptoms associated with rebound pulmonary hypertension, including dyspnea, dizziness, and asthenia. In clinical trials, one Class III primary pulmonary hypertension patient's death was judged attributable to the interruption of epoprostenol. Avoid abrupt withdrawal.

6 ADVERSE REACTIONS

6.1 Clinical Trials Experience

Because clinical trials are conducted under widely varying conditions, adverse reaction rates observed in the clinical trials of a drug cannot be directly compared to rates in the clinical trials of another drug and may not reflect the rates observed in practice.

During clinical trials, adverse events were classified as follows: (1) adverse events during dose initiation and escalation, (2) adverse events during chronic dosing, and (3) adverse events associated with the drug delivery system.

Adverse Events during Dose Initiation and Escalation

During early clinical trials, epoprostenol was increased in 2-ng/kg/min increments until the patients developed symptomatic intolerance. The most common adverse events and the adverse events that limited further increases in dose were generally related to vasodilation, the major pharmacologic effect of epoprostenol. The most common dose-limiting adverse events (occurring in ≥1% of patients) were nausea, vomiting, headache, hypotension, and flushing, but also include chest pain, anxiety, dizziness, bradycardia, dyspnea, abdominal pain, musculoskeletal pain, and tachycardia. Table 8 lists the adverse events reported during dose initiation and escalation in decreasing order of frequency.

Table 8: Adverse Events during Dose Initiation and Escalation
Adverse Events Occurring in ≥1% of Patients | Epoprostenol (n=391)
Flushing | 58%
Headache | 49%
Nausea/vomiting | 32%
Hypotension | 16%
Anxiety, nervousness, agitation | 11%
Chest pain | 11%
Dizziness | 8%
Bradycardia | 5%
Abdominal pain | 5%
Musculoskeletal pain | 3%
Dyspnea | 2%
Back pain | 2%
Sweating | 1%
Dyspepsia | 1%
Hypesthesia/paresthesia | 1%
Tachycardia | 1%

Adverse Events during Chronic Administration:

Interpretation of adverse events is complicated by the clinical features of PAH, which are similar to some of the pharmacologic effects of epoprostenol (e.g., dizziness, syncope). Adverse events which may be related to the underlying disease include dyspnea, fatigue, chest pain, edema, hypoxia, right ventricular failure, and pallor. Several adverse events, on the other hand, can clearly be attributed to epoprostenol. These include hypotension, bradycardia, tachycardia, pulmonary edema, bleeding at various sites, thrombocytopenia, headache, abdominal pain, pain (unspecified), sweating, rash, arthralgia, jaw pain, flushing, diarrhea, nausea and vomiting, flu-like symptoms, anxiety/nervousness, and agitation. In addition, chest pain, fatigue, and pallor have been reported during epoprostenol therapy, and a role for the drug in these events cannot be excluded.

Adverse Events during Chronic Administration for Idiopathic or Heritable PAH

In an effort to separate the adverse effects of the drug from the adverse effects of the underlying disease, Table 9 lists adverse events that occurred at a rate at least 10% greater on epoprostenol than on conventional therapy in controlled trials for idiopathic or heritable PAH.

Table 9: Adverse Events Regardless of Attribution Occurring in Patients with Idiopathic or Heritable PAH with ≥10% Difference between Epoprostenol and Conventional Therapy Alone
Adverse Event | Epoprostenol (n=52) | Conventional Therapy (n=54)
Occurrence More Common With Epoprostenol
General
Chills/fever/sepsis/flu-like symptoms | 25% | 11%
Cardiovascular
Tachycardia | 35% | 24%
Flushing | 42% | 2%
Gastrointestinal
Diarrhea | 37% | 6%
Nausea/vomiting | 67% | 48%
Musculoskeletal
Jaw pain | 54% | 0%
Myalgia | 44% | 31%
Nonspecific musculoskeletal pain | 35% | 15%
Neurological
Anxiety/nervousness/tremor | 21% | 9%
Dizziness | 83% | 70%
Headache | 83% | 33%
Hypesthesia, hyperesthesia, paresthesia | 12% | 2%

Thrombocytopenia has been reported during uncontrolled clinical trials in patients receiving epoprostenol.

Adverse Events during Chronic Administration for PAH/SSD

In an effort to separate the adverse effects of the drug from the adverse effects of the underlying disease, Table 10 lists adverse events that occurred at a rate at least 10% greater on epoprostenol in the controlled trial.

Table 10: Adverse Events Regardless of Attribution Occurring in Patients with PAH/SSD With ≥10% Difference Between Epoprostenol and Conventional Therapy Alone
Adverse Event | Epoprostenol (n=56) | Conventional Therapy (n=55)
Cardiovascular
Flushing | 23% | 0%
Hypotension | 13% | 0%
Gastrointestinal
Anorexia | 66% | 47%
Nausea/vomiting | 41% | 16%
Diarrhea | 50% | 5%
Musculoskeletal
Jaw pain | 75% | 0%
Pain/neck pain/arthralgia | 84% | 65%
Neurological
Headache | 46% | 5%
Skin and Appendages
Skin ulcer | 39% | 24%
Eczema/rash/urticaria | 25% | 4%

Although the relationship to epoprostenol administration has not been established, pulmonary embolism has been reported in several patients taking epoprostenol and there have been reports of hepatic failure.

Adverse Events Attributable to the Drug Delivery System

Chronic infusions of epoprostenol are delivered using a small, portable infusion pump through an indwelling central venous catheter. During controlled PAH trials of up to 12 weeks' duration, the local infection rate was about 18%, and the rate for pain was about 11%. During long-term follow-up, sepsis was reported at a rate of 0.3 infections/patient per year in patients treated with epoprostenol. This rate was higher than reported in patients using chronic indwelling central venous catheters to administer parenteral nutrition, but lower than reported in oncology patients using these catheters. Malfunctions in the delivery system resulting in an inadvertent bolus of or a reduction in epoprostenol were associated with symptoms related to excess or insufficient epoprostenol, respectively

6.2 Postmarketing Experience

In addition to adverse reactions reported from clinical trials, the following events have been identified during post-approval use of epoprostenol. Because they are reported voluntarily from a population of unknown size, estimates of frequency cannot be made. These events have been chosen for inclusion due to a combination of their seriousness, frequency of reporting, or potential causal connection to epoprostenol.

Blood and Lymphatic: Anemia, hypersplenism, pancytopenia, splenomegaly.

Cardiac: High output cardiac failure (consider dose reduction) [see Dosage and Administration (2.2), Warnings and Precautions (5.1), and Warnings and Precautions (5.3)].

Endocrine and Metabolic: Hyperthyroidism

7 DRUG INTERACTIONS

Additional reductions in blood pressure may occur when VELETRI is administered with diuretics, antihypertensive agents, or other vasodilators. When other antiplatelet agents or anticoagulants are used concomitantly, there is the potential for VELETRI to increase the risk of bleeding. However, patients receiving infusions of epoprostenol in clinical trials were maintained on anticoagulants without evidence of increased bleeding. In clinical trials, epoprostenol was used with digoxin, diuretics, anticoagulants, oral vasodilators, and supplemental oxygen.

In a pharmacokinetic substudy in patients with congestive heart failure receiving furosemide or digoxin in whom therapy with epoprostenol was initiated, apparent oral clearance values for furosemide (n=23) and digoxin (n=30) were decreased by 13% and 15%, respectively, on the second day of therapy and had returned to baseline values by day 87. The change in furosemide clearance value is not likely to be clinically significant. However, patients on digoxin may show elevations of digoxin concentrations after initiation of therapy with epoprostenol, which may be clinically significant in patients prone to digoxin toxicity.

8 USE IN SPECIFIC POPULATIONS

8.1 Pregnancy

Risk Summary

Limited published data from case series and case reports with VELETRI have not established a drug associated risk of major birth defects, miscarriage or adverse maternal or fetal outcomes when used during pregnancy. There are risks to the mother and fetus from untreated pulmonary arterial hypertension (see Clinical Considerations). In animal reproduction studies, pregnant rats and rabbits received epoprostenol sodium during organogenesis at exposures of 2.5 and 4.8 times the maximum recommended human dose (MRHD), respectively, and there was no effect on the fetus (see Data).

The estimated background risk of major birth defects and miscarriage for the indicated population is unknown. All pregnancies have a background risk of birth defect, loss, or other adverse outcomes. In the U.S. general population, the estimated background risk of major birth defects and miscarriage in clinically recognized pregnancies is 2% to 4% and 15% to 20%, respectively.

Clinical Considerations

Disease-Associated Maternal and/or Embryo/Fetal Risk

Pregnant women with untreated pulmonary arterial hypertension are at risk for heart failure, stroke, preterm delivery, and maternal and fetal death.

Data

Animal Data

Embryo-fetal development studies have been performed in rats and rabbits during organogenesis. Epoprostenol sodium doses up to 100 mcg/kg/day, a dose that was maternally toxic in rabbits but not in rats, (600 mcg/m^2/day in rats, 2.5 times the MRHD, and 1,180 mcg/m^2/day in rabbits, 4.8 times the MRHD based on body surface area), had no effect on the fetus.

In a postnatal development study, epoprostenol sodium was administered subcutaneously to female rats for 2 weeks prior to mating through weaning and to male rats for 60 days prior to and through mating at a male and female toxic dose of up to 100 mcg/kg/day (600 mcg/m^2/day, 2.5 times the MRHD based on body surface area). There was no effect on growth and development of the offspring.

8.2 Lactation

Risk Summary

There are no data on the presence of epoprostenol in either human or animal milk, the effects on the breastfed infant, or the effect on milk production.

The developmental and health benefits of breastfeeding should be considered along with the mother's clinical need for VELETRI and any potential adverse effects on the breastfed child from epoprostenol or from the underlying maternal condition.

8.4 Pediatric Use

Safety and effectiveness in pediatric patients have not been established.

8.5 Geriatric Use

Clinical studies of epoprostenol in pulmonary hypertension did not include sufficient numbers of subjects aged 65 and over to determine whether they respond differently from younger patients. Other reported clinical experience has not identified differences in responses between the elderly and younger patients. In general, dose selection for an elderly patient should be cautious, usually starting at the low end of the dosing range, reflecting the greater frequency of decreased hepatic, renal, or cardiac function and of concomitant disease or other drug therapy.

10 OVERDOSAGE

Signs and symptoms of excessive doses of epoprostenol during clinical trials are the expected dose-limiting pharmacologic effects of epoprostenol, including flushing, headache, hypotension, tachycardia, nausea, vomiting, and diarrhea. Treatment will ordinarily require dose reduction of epoprostenol.

One patient with secondary pulmonary hypertension accidentally received 50 mL of an unspecified concentration of epoprostenol. The patient vomited and became unconscious with an initially unrecordable blood pressure. Epoprostenol was discontinued and the patient regained consciousness within seconds. In clinical practice, fatal occurrences of hypoxemia, hypotension, and respiratory arrest have been reported following overdosage of epoprostenol.

Single intravenous doses of epoprostenol at 10 and 50 mg/kg (2,703 and 27,027 times the recommended acute phase human dose based on body surface area) were lethal to mice and rats, respectively. Symptoms of acute toxicity were hypoactivity, ataxia, loss of righting reflex, deep slow breathing, and hypothermia.

11 DESCRIPTION

Epoprostenol sodium is the sodium salt of epoprostenol, formulated as a sterile lyophilized powder for intravenous (IV) administration. Each vial of VELETRI contains epoprostenol sodium equivalent to either 0.5 mg (500,000 ng) or 1.5 mg (1,500,000 ng) epoprostenol, 50 mg arginine and 100 mg sucrose. Sodium hydroxide is added to adjust pH.

Epoprostenol (PGI2, PGX, prostacyclin), a metabolite of arachidonic acid, is a naturally occurring prostaglandin with potent vasodilatory activity and inhibitory activity of platelet aggregation.

Epoprostenol is (5Z,9a,11a,13E,15S)-6,9-epoxy-11,15-dihydroxyprosta-5,13-dien-1-oic acid. Epoprostenol sodium has a molecular weight of 374.45 and a molecular formula of C20H31NaO5. The structural formula is:

VELETRI is a white to off-white lyophilized powder material. It is reconstituted with Sterile Water for Injection, USP, or Sodium Chloride 0.9% Injection, USP.

The reconstituted solution of VELETRI has a pH ranging from 11 to 13 and is increasingly unstable at a lower pH.

12 CLINICAL PHARMACOLOGY

12.1 Mechanism of Action

Epoprostenol has 2 major pharmacological actions: (1) direct vasodilation of pulmonary and systemic arterial vascular beds, and (2) inhibition of platelet aggregation.

12.2 Pharmacodynamics

In animals, the vasodilatory effects reduce right- and left-ventricular afterload and increase cardiac output and stroke volume. The effect of epoprostenol on heart rate in animals varies with dose. At low doses, there is vagally mediated bradycardia, but at higher doses, epoprostenol causes reflex tachycardia in response to direct vasodilation and hypotension. No major effects on cardiac conduction have been observed. Additional pharmacologic effects of epoprostenol in animals include bronchodilation, inhibition of gastric acid secretion, and decreased gastric emptying.

12.3 Pharmacokinetics

Epoprostenol is rapidly hydrolyzed at neutral pH in blood and is also subject to enzymatic degradation. Animal studies using tritium-labeled epoprostenol have indicated a high clearance (93 mL/kg/min), small volume of distribution (357 mL/kg), and a short half-life (2.7 minutes). During infusions in animals, steady-state plasma concentrations of tritium-labeled epoprostenol were reached within 15 minutes and were proportional to infusion rates.

No available chemical assay is sufficiently sensitive and specific to assess the in vivo human pharmacokinetics of epoprostenol. The in vitro half-life of epoprostenol in human blood at 37°C and pH 7.4 is approximately 6 minutes; therefore, the in vivo half-life of epoprostenol in humans is expected to be no greater than 6 minutes. The in vitro pharmacologic half-life of epoprostenol in human plasma, based on inhibition of platelet aggregation, was similar for males (n=954) and females (n=1,024).

Tritium-labeled epoprostenol has been administered to humans in order to identify the metabolic products of epoprostenol. Epoprostenol is metabolized to 2 primary metabolites: 6-keto-PGF1α (formed by spontaneous degradation) and 6,15-diketo-13,14-dihydro-PGF1α (enzymatically formed), both of which have pharmacological activity orders of magnitude less than epoprostenol in animal test systems. The recovery of radioactivity in urine and feces over a 1-week period was 82% and 4% of the administered dose, respectively. Fourteen additional minor metabolites have been isolated from urine, indicating that epoprostenol is extensively metabolized in humans.

13 NONCLINICAL TOXICOLOGY

13.1 Carcinogenesis, Mutagenesis, Impairment of Fertility

Long-term studies in animals have not been performed to evaluate carcinogenic potential. A micronucleus test in rats revealed no evidence of mutagenicity. The Ames test and DNA elution tests were also negative, although the instability of epoprostenol makes the significance of these tests uncertain. Fertility was not impaired in rats given epoprostenol by subcutaneous injection at doses up to 100 mcg/kg/day (600 mcg/m^2/day, 2.5 times the recommended human dose [4.6 ng/kg/min or 245.1 mcg/m^2/day, IV] based on body surface area).

14 CLINICAL STUDIES

14.1 Clinical Trials in Pulmonary Arterial Hypertension (PAH)

Acute Hemodynamic Effects

Acute intravenous infusions of epoprostenol for up to 15 minutes in patients with idiopathic or heritable PAH or PAH associated with scleroderma spectrum of diseases (PAH/SSD) produce dose-related increases in cardiac index (CI) and stroke volume (SV) and dose-related decreases in pulmonary vascular resistance (PVR), total pulmonary resistance (TPR), and mean systemic arterial pressure (SAPm). The effects of epoprostenol on mean pulmonary arterial pressure (PAPm) were variable and minor.

Chronic Infusion in Idiopathic or Heritable PAH

Hemodynamic Effects

Chronic continuous infusions of epoprostenol in patients with idiopathic or heritable PAH were studied in 2 prospective, open, randomized trials of 8 and 12 weeks' duration comparing epoprostenol plus conventional therapy to conventional therapy alone. Dosage of epoprostenol was determined as described in Dosage and Administration (2) and averaged 9.2 ng/kg/min at study's end. Conventional therapy varied among patients and included some or all of the following: anticoagulants in essentially all patients; oral vasodilators, diuretics, and digoxin in one half to two thirds of patients; and supplemental oxygen in about half the patients. Except for 2 New York Heart Association (NYHA) functional Class II patients, all patients were either functional Class III or Class IV. As results were similar in the 2 studies, the pooled results are described.

Chronic hemodynamic effects were generally similar to acute effects. Increases in CI, SV, and arterial oxygen saturation and decreases in PAPm, mean right atrial pressure (RAPm), TPR, and systemic vascular resistance (SVR) were observed in patients who received epoprostenol chronically compared to those who did not. Table 11 illustrates the treatment-related hemodynamic changes in these patients after 8 or 12 weeks of treatment.

Table 11: Hemodynamics during Chronic Administration of Epoprostenol in Patients with Idiopathic or Heritable PAH
 | Baseline |  | Mean Change from Baseline at End of Treatment Period [At 8 weeks: Epoprostenol N=10, conventional therapy N=11 (N is the number of patients with hemodynamic data). At 12 weeks: Epoprostenol N=38, conventional therapy N=30 (N is the number of patients with hemodynamic data).]
Hemodynamic Parameter | Epoprostenol (N=52) | Standard Therapy (N=54) | Epoprostenol (N=48) | Standard Therapy (N=41)
CI (L/min/m^2) | 2.0 | 2.0 | 0.3 [Denotes statistically significant difference between Epoprostenol and conventional therapy groups.] | -0.1
PAPm (mmHg) | 60 | 60 | -5 | 1
PVR (Wood U) | 16 | 17 | -4 | 1
SAPm (mmHg) | 89 | 91 | -4 | -3
SV (mL/beat) | 44 | 43 | 6 | -1
TPR (Wood U) | 20 | 21 | -5 | 1
CI=cardiac index, PAPm=mean pulmonary arterial pressure, PVR=pulmonary vascular resistance, SAPm=mean systemic arterial pressure, SV=stroke volume, TPR=total pulmonary resistance.

These hemodynamic improvements appeared to persist when epoprostenol was administered for at least 36 months in an open, nonrandomized study.

Clinical Effects

Statistically significant improvement was observed in exercise capacity, as measured by the 6-minute walk test in patients receiving continuous intravenous epoprostenol plus conventional therapy (N=52) for 8 or 12 weeks compared to those receiving conventional therapy alone (N=54). Improvements were apparent as early as the first week of therapy. Increases in exercise capacity were accompanied by statistically significant improvement in dyspnea and fatigue, as measured by the Chronic Heart Failure Questionnaire and the Dyspnea Fatigue Index.

Survival was improved in NYHA functional Class III and Class IV patients with idiopathic or heritable PAH treated with epoprostenol for 12 weeks in a multicenter, open, randomized, parallel study. At the end of the treatment period, 8 of 40 (20%) patients receiving conventional therapy alone died, whereas none of the 41 patients receiving epoprostenol died (p=0.003).

Chronic Infusion in PAH/Scleroderma Spectrum of Diseases (SSD)

Hemodynamic Effects

Chronic continuous infusions of epoprostenol in patients with PAH/SSD were studied in a prospective, open, randomized trial of 12 weeks' duration comparing epoprostenol plus conventional therapy (N=56) to conventional therapy alone (N=55). Except for 5 NYHA functional Class II patients, all patients were either functional Class III or Class IV. Dosage of epoprostenol was determined as described in Dosage and Administration (2) and averaged 11.2 ng/kg/min at study's end. Conventional therapy varied among patients and included some or all of the following: anticoagulants in essentially all patients, supplemental oxygen and diuretics in two thirds of the patients, oral vasodilators in 40% of the patients, and digoxin in a third of the patients. A statistically significant increase in CI, and statistically significant decreases in PAPm, RAPm, PVR, and SAPm after 12 weeks of treatment were observed in patients who received epoprostenol chronically compared to those who did not. Table 12 illustrates the treatment-related hemodynamic changes in these patients after 12 weeks of treatment.

Table 12: Hemodynamics during Chronic Administration of Epoprostenol in Patients with PAH/SSD
 | Baseline |  | Mean Change from Baseline at 12 Weeks
Hemodynamic Parameter | Epoprostenol (N=56) | Conventional Therapy (N=55) | Epoprostenol (N=50) | Conventional Therapy (N=48)
CI (L/min/m^2) | 1.9 | 2.2 | 0.5 [Denotes statistically significant difference between Epoprostenol and conventional therapy groups (N is the number of patients with hemodynamic data).] | -0.1
PAPm (mmHg) | 51 | 49 | -5 | 1
RAPm (mmHg) | 13 | 11 | -1 | 1
PVR (Wood U) | 14 | 11 | -5 | 1
SAPm (mmHg) | 93 | 89 | -8 | -1
CI=cardiac index, PAPm=mean pulmonary arterial pressure, RAPm=mean right atrial pressure, PVR=pulmonary vascular resistance, SAPm=mean systemic arterial pressure.

Clinical Effects

Statistically significant improvement was observed in exercise capacity, as measured by the 6-minute walk, in patients receiving continuous intravenous epoprostenol plus conventional therapy for 12 weeks compared to those receiving conventional therapy alone. Improvements were apparent in some patients at the end of the first week of therapy. Increases in exercise capacity were accompanied by statistically significant improvements in dyspnea and fatigue, as measured by the Borg Dyspnea Index and Dyspnea Fatigue Index. At week 12, NYHA functional class improved in 21 of 51 (41%) patients treated with epoprostenol compared to none of the 48 patients treated with conventional therapy alone. However, more patients in both treatment groups (28/51 [55%] with epoprostenol and 35/48 [73%] with conventional therapy alone) showed no change in functional class, and 2/51 (4%) with epoprostenol and 13/48 (27%) with conventional therapy alone worsened. Of the patients randomized, NYHA functional class data at 12 weeks were not available for 5 patients treated with epoprostenol and 7 patients treated with conventional therapy alone.

No statistical difference in survival over 12 weeks was observed in PAH/SSD patients treated with epoprostenol as compared to those receiving conventional therapy alone. At the end of the treatment period, 4 of 56 (7%) patients receiving epoprostenol died, whereas 5 of 55 (9%) patients receiving conventional therapy alone died.

No controlled clinical trials with epoprostenol have been performed in patients with pulmonary hypertension associated with other diseases.

16 HOW SUPPLIED/STORAGE AND HANDLING

16.1 How Supplied

VELETRI is supplied as a sterile lyophilized material in 10 mL vials.

10 mL vial with a white flip-off seal containing epoprostenol sodium equivalent to 0.5 mg (500,000 ng) epoprostenol, is packaged in carton of 1 vial (NDC 66215-403-01).

10 mL vial with a red flip-off seal containing epoprostenol sodium equivalent to 1.5 mg (1,500,000 ng) epoprostenol, is packaged in carton of 1 vial (NDC 66215-402-01).

Store the vials of VELETRI at 68° to 77°F (20° to 25°C) [see USP Controlled Room Temperature].

16.2 Storage and Stability

Unopened vials of VELETRI are stable until the date indicated on the package when stored at 68° to 77°F (20° to 25°C). The unopened vial should be kept in the carton and not exposed to direct sunlight.

Use after reconstitution and immediate dilution to final concentration can be found in Dosage and Administration (2.4) Reconstitution, Table 1: Maximum duration of administration (hours) at room temperature (77°F/25°C) of fully diluted solutions in the drug delivery reservoir.

Inspect parenteral drug products for particulate matter and discoloration prior to administration whenever solution and container permit. If either occurs, do not administer.

17 PATIENT COUNSELING INFORMATION

Patients receiving VELETRI should receive the following information.

VELETRI must be reconstituted as directed using only Sterile Water for Injection, USP, or Sodium Chloride 0.9% Injection, USP. VELETRI is infused continuously through a permanent indwelling central venous catheter via a small, portable infusion pump. Thus, therapy with VELETRI requires commitment by the patient to drug reconstitution, drug administration, and care of the permanent central venous catheter. Patients must adhere to sterile technique in preparing the drug and in the care of the catheter, and even brief interruptions in the delivery of VELETRI may result in rapid symptomatic deterioration. A patient's decision to receive VELETRI should be based upon the understanding that there is a high likelihood that therapy with VELETRI will be needed for prolonged periods, possibly years. The patient's ability to accept and care for a permanent intravenous catheter and infusion pump should also be carefully considered.

Manufactured for:
Actelion Pharmaceuticals US, Inc.
a Janssen Pharmaceutical Company
Titusville, NJ 08560, USA

For patent information: www.janssenpatents.com

© 2008 – 2019 Actelion Pharmaceuticals US, Inc.

JN20220728

PRINCIPAL DISPLAY PANEL - 0.5 mg Vial Carton

NDC 66215-403-01
Single-dose Vial
Discard unused portion.

VELETRI®
(epoprostenol) for Injection

0.5 mg (500,000 ng)/vial

Sterile, Lyophilized Product
For Intravenous Infusion Only

Rx only

janssen

PRINCIPAL DISPLAY PANEL - 1.5 mg Vial Carton

NDC 66215-402-01
Single-dose Vial
Discard unused portion.

VELETRI®
(epoprostenol) for Injection

1.5 mg (1,500,000 ng)/vial

Sterile, Lyophilized Product
For Intravenous Infusion Only

Rx only

janssen